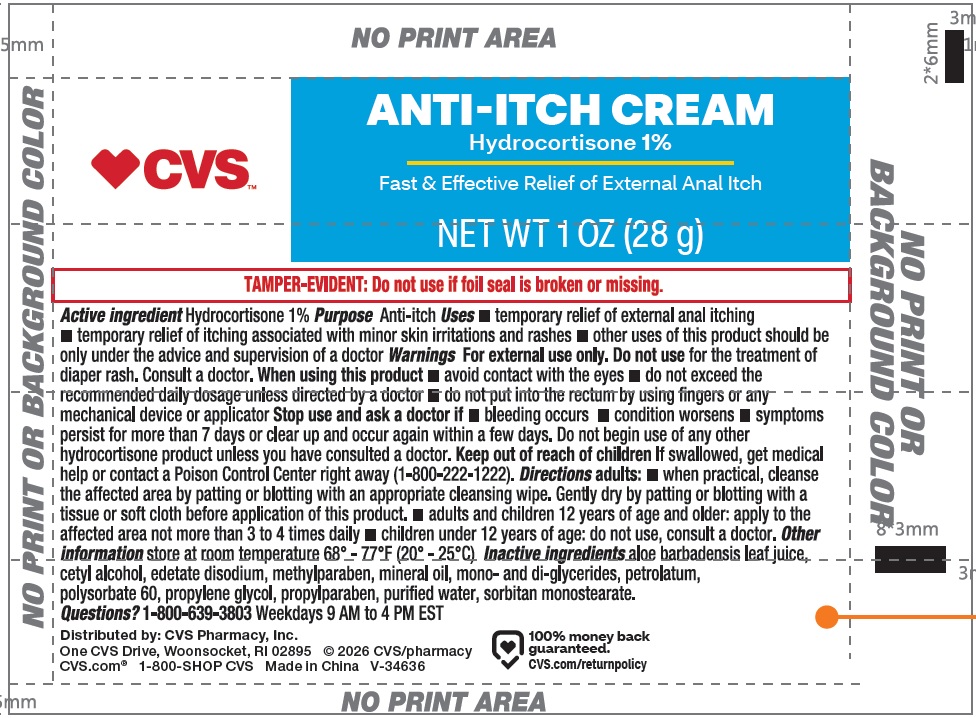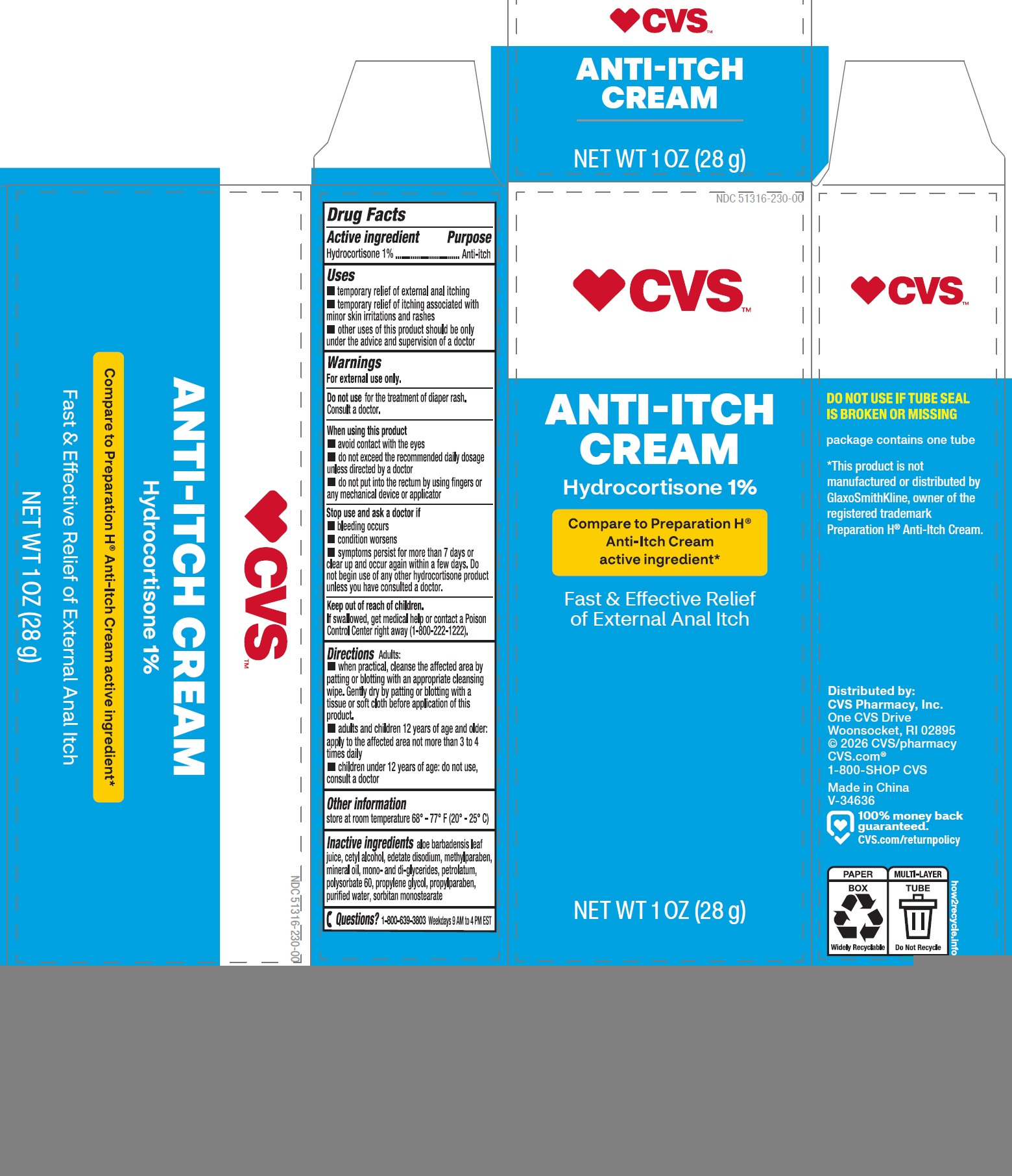 DRUG LABEL: HYDROCORTISONE
NDC: 51316-230 | Form: CREAM
Manufacturer: CVS PHARMACY, INC
Category: otc | Type: HUMAN OTC DRUG LABEL
Date: 20260202

ACTIVE INGREDIENTS: HYDROCORTISONE 10 mg/1 g
INACTIVE INGREDIENTS: ALOE VERA LEAF; CETYL ALCOHOL; EDETATE DISODIUM; METHYLPARABEN; MINERAL OIL; PETROLATUM; POLYSORBATE 60; PROPYLENE GLYCOL; PROPYLPARABEN; WATER; SORBITAN MONOSTEARATE

HYDROCORTISONE CREAM

Active ingredient

Hydrocortisone 1%

Purpose

Anti-itch

Uses

- temporary relief of external anal itching
- temporary relief of itching associated with minor skin irritations and rashes
- other uses of this product should be only under the advice and supervision of a doctor

Warnings

For external use only.

Do not use

for the treatment of diaper rash. Consult a doctor.

When using this product

- avoid contact with the eyes
- do not exceed the recommended daily dosage unless directed by a doctor
- do not put into the rectum by using fingers or any mechanical device or applicator

Stop use and ask a doctor if

- bleeding occurs
- condition worsens
- symptoms persist for more than 7 days or clear up and occur again within a few days. Do not begin use of any other hydrocortisone product unless you have consulted a doctor.

Keep out of reach of children.

If swallowed, get medical help or contact a Poison Control Center right away (1-800-222-1222).

Directions

Adults:

- when practical, cleanse the affected area by patting or blotting with an appropriate cleansing wipe. Gently dry by patting or blotting with a tissue or soft cloth before application of this product.
- adults and children 12 years of age and older: apply to the affected area not more than 3 to 4 times daily
- children under 12 years of age: do not use, consult a doctor

Other information

store at room temperature 68° - 77° F (20° - 25° C)

Inactive ingredients

aloe barbadensis leaf juice, cetyl alcohol, edetate disodium, methylparaben, mineral oil, mono- and di-glycerides, petrolatum, polysorbate 60, propylene glycol, propylparaben, purified water, sorbitan monostearate

Questions?

1-800-639-3803 Weekdays 9 AM to 4 PM EST